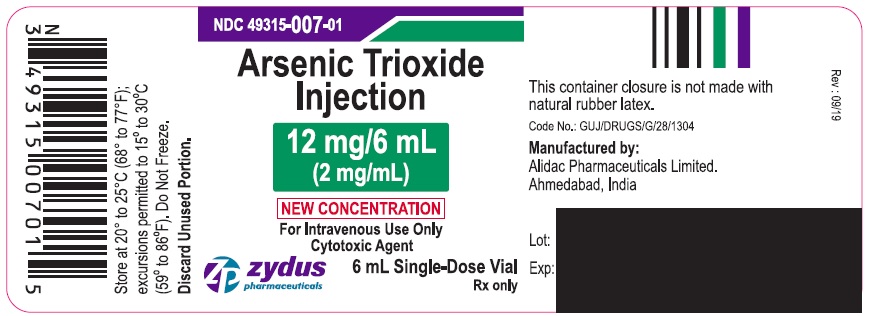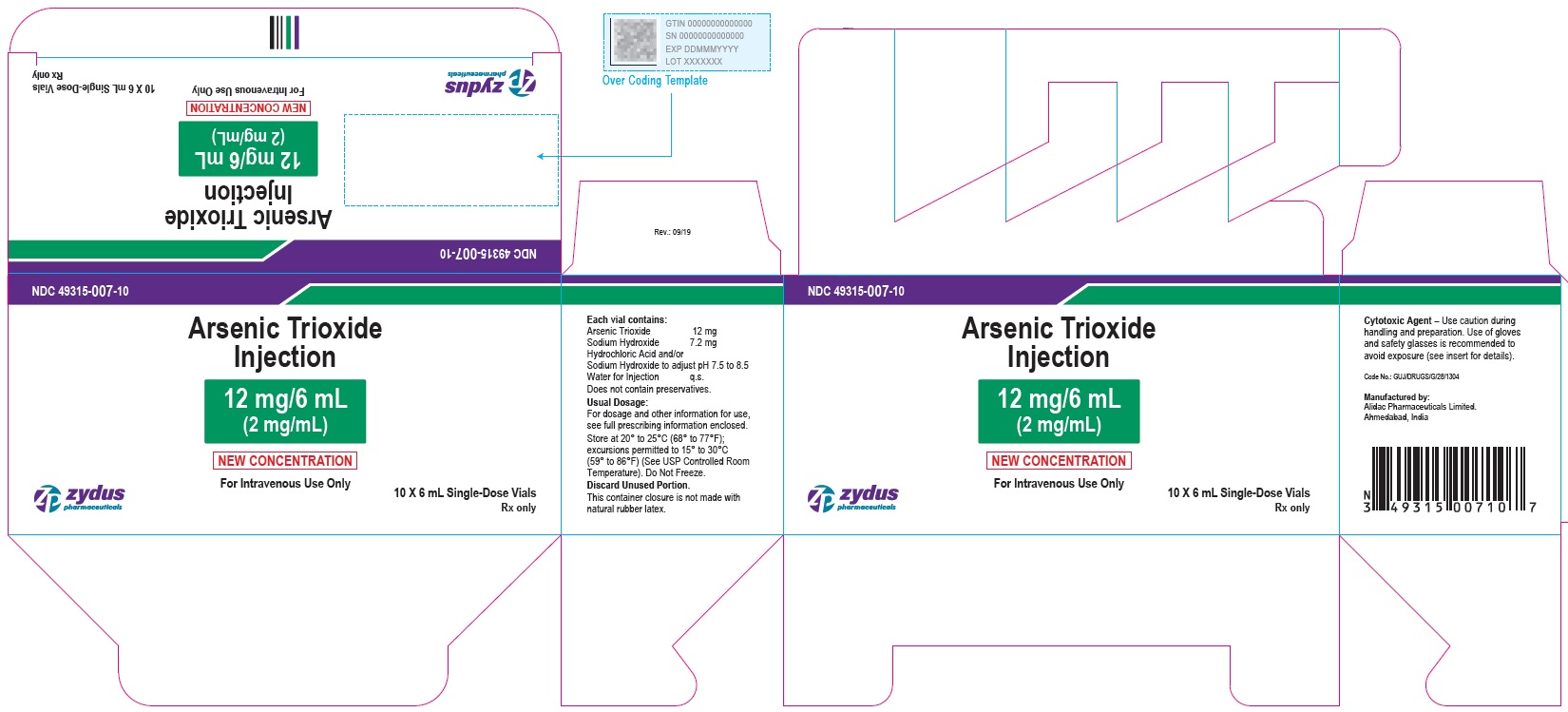 DRUG LABEL: Arsenic trioxide
NDC: 49315-007 | Form: INJECTION, SOLUTION
Manufacturer: Zydus Lifesciences Limited
Category: prescription | Type: HUMAN PRESCRIPTION DRUG LABEL
Date: 20221105

ACTIVE INGREDIENTS: ARSENIC TRIOXIDE 2 mg/1 mL
INACTIVE INGREDIENTS: SODIUM HYDROXIDE; HYDROCHLORIC ACID; WATER

ARSENIC TRIOXIDE INJECTION

PRINCIPAL DISPLAY PANEL - Vial Label

NDC 49315-007-01

Arsenic Trioxide Injection

12 mg/6 mL

(2 mg/mL)

NEW CONCENTRATION

For Intravenous Use Only

Cytotoxic Agent

6 mL Single-Dose Vial

Rx only

Zydus Pharmaceuticals

PRINCIPAL DISPLAY PANEL - Carton Label

NDC 49315-007-10

Arsenic Trioxide Injection

12 mg/6 mL

(2 mg/mL)

NEW CONCENTRATION

For Intravenous Use Only

10 X 6 mL Single-Dose Vials

Rx only

Zydus Pharmaceuticals